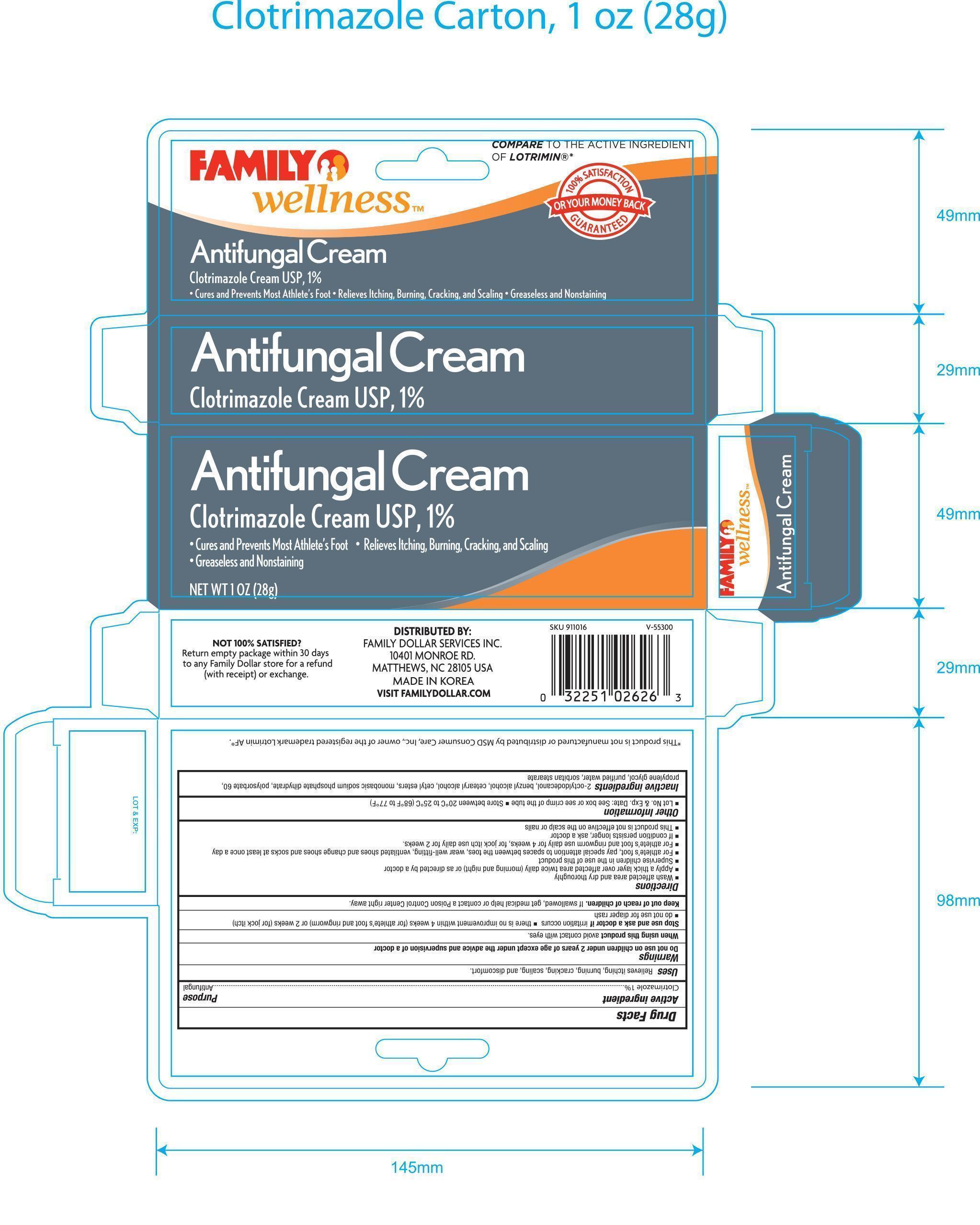 DRUG LABEL: Family Wellness Antifungal
NDC: 55319-626 | Form: CREAM
Manufacturer: Family Dollar
Category: otc | Type: HUMAN OTC DRUG LABEL
Date: 20140121

ACTIVE INGREDIENTS: CLOTRIMAZOLE 10 mg/1 g
INACTIVE INGREDIENTS: 2-OCTYLDODECYL PALMITATE; BENZYL ALCOHOL; CETEARYL BEHENATE; CETYL ESTERS WAX; MAGNESIUM PHOSPHATE, MONOBASIC, DIHYDRATE; POLYSORBATE 60; PROPYLENE GLYCOL; WATER; PEG-60 SORBITAN STEARATE

Active Ingredient Purpose

Clotrimazole 1%............................................... Antifungal

Uses

Relieves itching, burning, cracking, scaling, and discomfort

Warnings

Do not use on children under 2 years of age except under the advice and supervision of a doctor

When using this product avoid contact with eyes

Stop use and ask a doctor if:

- irritation occurs
- there is no improvement within 4 weeks (for athlete's food and ringwood) or 2 weeks (for jock itch)
- do not use for diaper rash

Keep out of reach of children.

If swallowed, get medical help or contact a Poision Control Center right away.

Directions

- Wash affected area and dry thoroughly
- Apply a thick layer over affected area twice daily (morning and night) or as directed by a doctor
- Supervise children in the use of this product
- For athlete's foot, pay special attention to spaces between the toes, wear well-fitting, ventilated shoes and change shoes and socks at least once a day
- For athlete's foot and ringworm use daily for 4 weeks, for jock itch use daily for 2 weeks
- In condition persists longer, ask a doctor
- This product is no effective on the scalp or nails

Other information

- Lot No. & Exp. Date: See box or see crimp of the tube
- Store between 20°C to 25°C (68°F to 77°F)

Inactive ingredients

2-octyldodecanol, benzyl alcohol, cetearyl alcohol, cetyl esters, monobasic sodium phosphate dihydrate, polysorbate 60, proylene glycol, purified water, sorbitan stearate

DOSAGE AND ADMINISTRATION

DISTRIBUTED BY:

FAMILY DOLLAR SERVICES INC.

10401 MONROE RD.

MATTHEWS, NC 28105 USA